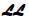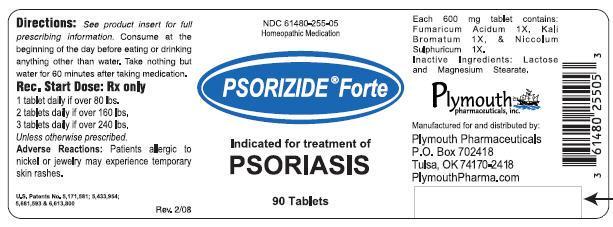 DRUG LABEL: Psorizide Forte
NDC: 61480-255 | Form: TABLET
Manufacturer: PLYMOUTH HEALTHCARE PRODUCTS LLC
Category: homeopathic | Type: HUMAN PRESCRIPTION DRUG LABEL
Date: 20251120

ACTIVE INGREDIENTS: NICKEL SULFATE 1 [hp_X]/1 1; POTASSIUM BROMIDE 1 [hp_X]/1 1; FUMARIC ACID 1 [hp_X]/1 1

PSORIZIDE®Forte

CAUTION

Federal law prohibits dispensing without a prescription.

DESCRIPTION

PSORIZIDE®Forte is a biochemical homeopathic medication indicated for the treatment of contact dermatitis due to nickel (metal/jewelry allergy), dyshidrotic hand/foot eczema, and mild to severe psoriasis.^1-3The active ingredients in each PSORIZIDE®Forte tablet consist of the following: Fumaric Acid (Fumaricum Acidum) 1X, Potassium Bromide (Kali Bromatum) 1X, and Nickel Sulphate (Niccolum Sulphuricum) 1X. These drug ingredients are listed in the Homoeopathic Pharmacopoeia of the United States (HPUS).^4

Inactive ingredients: Lactose and Magnesium Stearate.

Pharmacological Class:Homeopathic drug.

Dosage form:Oral 600 mg scored tablet. May be swallowed whole, chewed or dissolved in the mouth and swallowed.

CLINICAL PHARMACOLOGY

The active ingredients in PSORIZIDE®Forte are simple biochemical compounds. The exact mechanism of action is unknown; however, it is believed PSORIZIDE®Forte addresses a primary genetic biochemical defect.^5

FUMARIC ACIDis a naturally occurring four carbon organic acid important in the Krebs cycle. This biochemical pathway is of central importance to energy production. Each tablet contains approximately 30 mg fumaric acid (calculated). Fumaric Acid has many uses, including use as a food additive (GRAS) and as a chelating agent.^13The use of fumaric acid and its derivatives (esters) as a treatment for psoriasis is increasing worldwide.^14-20Very little is known about its clinical pharmacology; however, dose dependant inhibitory effects on keratinocyte proliferation have been demonstrated.^16,21

POTASSIUM BROMIDEdissolves and dissociates in the digestive tract into its ionic constituents. Each tablet contains approximately 15 mg bromide (calculated). Ionic bromide is rapidly and completely absorbed from the intestine and distributed almost exclusively into the extracellular fluids.^11,12Bromide is eliminated by the kidneys and the elimination half-life is 11-12 days. "Once a day" dosing will lead to a steady state concentration in about seven weeks.^11

NICKEL SULPHATEdissolves and dissociates in the digestive tract into its ionic constituents. Each tablet contains approximately 1.0 mg of ionic nickel (calculated). According to studies, 15% to 50% of ionic nickel is absorbed on a fasted stomach.^6Food markedly decreases the rate and extent of nickel absorption.^7,8Clinical studies show that serum concentrations of nickel are variable among patients after administering the same dose.^9Peak serum nickel concentration is reached about two hours after oral administration. "Once a day" dosing leads to steady state serum concentrations in approximately one week. Nickel is in its highly stable divalent cation state and is therefore not expected to be metabolized to any significant degree in the body. Absorbed nickel is primarily excreted in the urine and elimination half-life is about 21 hours.^7,9Renal clearance is rapid and efficient, and nickel does not accumulate in the body.^10

CLINICAL STUDIES

A variety of controlled clinical studies have been performed using various sources of both nickel and bromide in over 300 subjects. Clinical efficacy and safety have been documented in a significant number of subjects. Published and unpublished reports are available upon request.^22,23,32

INDICATIONS

PSORIZIDE®Forte is indicated for the treatment of contact dermatitis due to nickel (metal/jewelry allergy,) dyshidrotic hand/foot eczema, and mild to severe psoriasis. It has been found to work well with a variety of combination therapies. Eczema, seborrhea and a variety of chronic pruritic inflammatory dermatoses generally respond well also.

CONTRAINDICATIONS

Although there are no known contraindications, patients who are allergic to any PSORIZIDE®Forte ingredient should consult a physician prior to taking the medication. (Refer to Section on Hypersensitivity)

WARNING

Do not use if imprinted seal under bottle cap is missing or broken. Do not use if pregnant or nursing. If allergic to nickel or metal objects such as jewelry, see PRECAUTIONSfor hypersensitivity information. Lactose intolerant patients may have gastrointestinal difficulty. This has very rarely been reported at the doses used.

PRECAUTIONS

Carefully adjust dosage to weight when treating young children. Use cautiously in setting of kidney disease. (see Dosage and Administration) If skin rash appears or if nervous symptoms persist, recur frequently, or are unusual, discontinue use.

Hypersensitivity

Caution should be used when administering to patients with a history of contact sensitivity to nickel (common metal exposure). Nickel allergy may be confirmed by a positive nickel patch test. Most patients with positive nickel allergy history or a positive nickel patch test do nothave any untoward reaction to administration of PSORIZIDE®Forte. However, if there is a history of nickel sensitivity, begin with a very low dose and slowly increase over a period of six weeks as tolerated. Progressive G.I. absorption allows desensitization to occur.^8

Nickel desensitization schedule:
Week | Amount of Time to Take Medication Prior to Breakfast
Week 1 | 1 tablet With Breakfast
Week 2 | 1 tablet 15 min Prior
Week 3 | 1 tablet 30 min Prior
Week 4 | 1 tablet 45 min Prior
Week 5 | 1 tablet 1 hour Prior
Week 6 and thereon | 2 tablets 1 hour Prior

If new pruritic rashes occur or persist, discontinue PSORIZIDE®Forte and treat appropriately. Do not use if there is a history of extra-cutaneous hypersensitivity to nickel or any ingredient in PSORIZIDE®Forte.

Information for patients

Patients using PSORIZIDE®Forte should receive the following information and instructions:

1. This medication is to be used only as directed by a physician.
2. It is important to take orally at the beginning of the day on an empty stomach (or any convenient time after having taken nothing but water for at least 7 hours) and to eat or drink nothing but water for one hour afterwards to avoid interference with absorption.

Drug Interactions

There are no known drug interactions.

Carcinogenesis, mutagenesis, and impairment of fertility

No studies have been done on the carcinogenesis, mutagenesis, or impairment of fertility of PSORIZIDE®Forte. No carcinogenesis or mutagenesis has been reported in multiple animal studies for oral administration of fumaric acid and soluble nickel and bromide salts (active ingredients) even at very high doses.^24-27

Effects of fumaric acid

It is not listed as a carcinogen by ACGIH, IARC, NIOSH, NTP, or OSHA.^26It is a GRAS substance (generally recognized as safe) and is commonly used in food processing.

Effects of soluble potassium bromide

KBr is not listed as a carcinogen by the NTP, IARC, and OSHA.^28

Effects of soluble nickel sulphate

Studies on experimental animals have never indicated that nickel, at any dose, is a carcinogen when introduced to the body orally. Furthermore, Nickel sulphate and other highly water soluble nickel salts, have never been known to induce carcinogenesis via any route of introduction including: oral, inhalation, cutaneous, IM, or IP.^10-12,27No adverse effects were noted on fertility or reproduction in a 3-generational study of albino Wistar rats fed up to 1000 ppm Ni per day, which is equivalent to 50 mg/kg body weight per day Ni.^27

Pregnancy

Pregnancy category C

Animal reproduction studies have not been conducted with PSORIZIDE®Forte. PSORIZIDE®Forte should not be given to a pregnant woman.

Nursing mothers

It is not known whether this drug is secreted in human milk. However, since many drugs are secreted in human milk, caution should be exercised when PSORIZIDE®Forte is administered to a nursing woman.

Pediatric use

Carefully adjust dosage to weight when treating young children.

ADVERSE REACTIONS

PSORIZIDE®Forte contains low doses of active ingredients. Therefore there are minimal known side effects.

(see PRECAUTIONSfor hypersensitivity information)

OVERDOSAGE

Fumaric acid toxicity

The oral rat LD50is 9300mg/kg.^26This is 3800 times the maximum dose recommended for PSORIZIDE®Forte.

Potassium bromide toxicity

Indications of toxicity due to oral overdosage of bromide may include nausea and vomiting, apathy, disturbed coordination, loss of memory, drowsiness, loss of emotional control, agitation, hallucination, tremors, depressed reflexes, stupor, and coma. Acute toxic reactions in humans have been reported at doses as low as 1000mg.^31This level is 67 times the dose received in one tablet of PSORIZIDE®Forte.

Nickel sulphate toxicity

The oral rat LD50for nickel sulphate hexahydrate is 275mg/kg.^29Symptoms of toxicity due to oral overdosage of nickel sulphate may include nausea, vomiting, abdominal discomfort, diarrhea, giddiness, lassitude, headaches, cough, and shortness of breath.^30The lowest observed transitory toxic effects from human ingestion of soluble nickel salts is approximately 8 mg nickel/kg body weight.^30This is 138 times the maximum dose recommended for PSORIZIDE®Forte (see below).

DOSAGE AND ADMINISTRATION

Absorption of nickel sulphate is variable among individuals . For maximum absorption, tablets should be taken orally at the beginning of the day(or any convenient time after having taken nothing but water for at least 7 hours). Take nothing but water for one hour after taking medication to aid absorption.

Weight | Starting Dose | Max Daily Dose
40-80 lbs | ½ tablet | 1 ½ tablet
80-120 lbs | 1 tablet | 3 tablets
120-160 lbs | 1 ½ tablets | 4 ½ tablets
160-200 lbs | 2 tablets | 6 tablets
200-240 lbs | 2 ½ tablets | 7 ½ tablets
Over 240 lbs | 3 tablets | 9 tablets

In the setting of renal impairment

Dosage should be adjusted and serum nickel and bromide levels should be followed. Steady state trough level should be drawn priorto ingesting the day's dose after one week of dosing or at appropriate intervals. Target trough serum nickel level is 30-60 mcg/L. (Caution: post dose peak levels are unreliable.)

Maintenance phase

In order to maintain symptomatic relief, medication may be continued at the same or reduced initial phase dose level. Treatment duration depends on the individual. For allergic nickel dermatitis, continue 2 tablets 1 hour prior to breakfast for weeks 7 – 16. (Refer to Hypersensitivity section above). Some patients may require continued or intermittent repeated treatment to maintain nickel desensitization.

INACTIVE INGREDIENTS

Lactose and magnesium stearate.

HOW SUPPLIED

Scored tablets, off white in color with green speckles, with imprinted on one side and a score on the other, in child-resistant and tamperresistant bottles of 90 . NDC 61480-255-05

REFERENCES

1. Reckeweg, Hans-Heinrich, Materia Medica, 1983, first English edition.
2. Boericke, William, Materia Medica with Reperatory, 1927, ninth edition.
3. Clarke, John Henry, A Dictionary of Practical Materia Medica, 1921, reprint edition 1996.
4. The Homeopathic Pharmacopoeia of the United States (HPUS), December 2000 edition, Falls Church, Virginia.
5. Kiehl R, Ionescu G, A Defective Purine Nucleotide Synthesis Pathway in Psoriatic Patients, Acta Derm Venereol (stockh), 1992, 72:253-255.
6. Sunderman FW Jr. Biological monitoring of nickel in humans. Scand J. Work Environ Health 1993; 19 suppl 1:34-38.
7. Sunderman FW Jr., Hopfer SM, Sweeney KR, Marcus AH, Most BM, Creason J. Ncikel absorption and kinetics in human volunteers. P.S.E.B.M. 1989; 191:5-11.
8. Solomons NW, Viteri F, Shuler TR, Nielsen FH, Bioavailability of nickel in man: Effects of foods and chemically-defined dietary constituents on the absorption of inorganic nickel. J Nutr 1982; 112:39-50.
9. Christensen OB, Lagesson V. Nickel concentration of blood and urine after oral administration. Annals of Clinical and Laboratory Science 1981;2(2);119-125.
10. Nielsen FH. Is nickel nutritionally important? Nutrition Today 1993; 28 (1):14-19.
11. Vaiseman N. Koren G. Pencharz P. Pharmacokinetics of oral and intravenous bromide in normal volunteers. Clinical Toxicology 1986;24(5):403-413.
12. Van Leeuwen FXR, Sangster B. The toxicology of bromide ion. CRC Critical Reviews in Toxicology 1987; 18(3): 189-213.
13. Wade A, Weller PJ Handbook of Pharmaceutical Excipients 2ndedition, American Pharmaceutical Association, 1994.
14. Parfitts K, editor, Martindale: The complete Drug Reference, 1999, 32ndedition, Pharmaceutical Press, London.
15. Nieboer C, et al, Fumaric Acid Therapy in Psoriasis, Dermatologica, 1990; 181:33-37
16. Mrowietz U, et al, Treatment of severe psoriasis with fumaric acid esters: scientific background and guidelines for therapeutic use, Br J Dermatol 1999;141:424-429.
17. Mrowietz U, et al, Treatment of psoriasis with fumaric acid esters, Br J Dermatol 1998; 138:456-460.
18. Kolbach DN, Nieboer C, Fumaric Acid Therapy in Psoriasis, J Am Acad Dermatol 1992; 27: 769-771.
19. Altmeyer P, et al, Antipsoriatic Effect of Fumaric Acid Derivatives, J Am Acad Dermatol 1994; 30:997-981.
20. Nugteren – Huying WM, etal, Fumaric Acid Therapy for Psoriasis, J Am Acad Dermatol 1990; 22: 311-312.
21. Thio, HB, et al, Fumaric Acid Derivatives… Inhibit the proliferation of Human Keratinocytes, Br J Dermatol 1994; 131: 856-866.
22. Smith SA. Oral supplementation of nickel and bromide in psoriasis vulgaris using nickel sulfate and sodium bromide. 1995 (unpublished report).
23. Smith SA, et al, Improvement of Psoriasis Vulgaris with Oral Nickel Dibromide. Archives of Dermatology 1997; 133:661-663.
24. US EPA, Environmental Criteria and Assessment Office, Office of Health and Environmental Assessment. Drinking water quantification of toxicological effects for nickel. ECAO-CIN-443. US FDA, Center for Food Safety and Applied Nutrition. Guidance document for nickel in shellfish. 1993.
25. IARC Monograph on the Evaluation of Carcinogenic Risk of Chemicals to Man. IRC Publication #11, Lyon, France 1976.
26. MSDS Fumaric Acid. Acros Organics, Fair Lawn, N.J., Revised 8/2000.
27. Ambrose AM, Larson PS, Borsellaca FJ, and Hennigar GR, JR. Long term toxicologic assessment of nickel in rats and dogs. Journal of Food and Science and Technology 1976;13:181-187.
28. MSDS Sheet No. 247 Potassium Bromide, Schenectady, NY: Genium Publishing Corp 1991.
29. MSDS Sheet No. 37 Nickel Sulfate, Schenectady, NY: Genium Publishing Corp 1993.
30. Sunderman FW Jr., Dingle B, Hopfer SM, and Swift T. Acute nickel toxicity in electroplating workers who accidentally ingested a solution of nickel sulfate and nickel chloride. American Journal of Industrial Medicine 1988; 14:257-266.
31. Martindale: The Extra Pharmacopoeia, 27thed. Wade A, editor. The Pharmaceutical Press: London, 1977, pp 273-274.
32. Smith SA, Baker AE, etal. Effective Treatment of Seborrheic Dermatitis Using a Low Dose, Oral Homeopathic Medication… Alt Med Rev 2002; 7, pp59-67, 1991.

RxSales@PlymouthPharmaceuticals.com

www.PlymouthPharmaceuticals.com

Plymouth Pharmaceuticals Inc. dba LOMA LUX Laboratories; P.O. BOX 702418; Tulsa, OK 74170-2418

Phone 800.316.9636, 918.664.9882, Fax 918.664.9884

Revised 1.10.07 TS

PRINCIPAL DISPLAY PANEL - 90 Tablet Label

NDC 61480-255-05
Homeopathic Medication

PSORIZIDE®Forte

Indicated for treatment of
PSORIASIS

90 Tablets